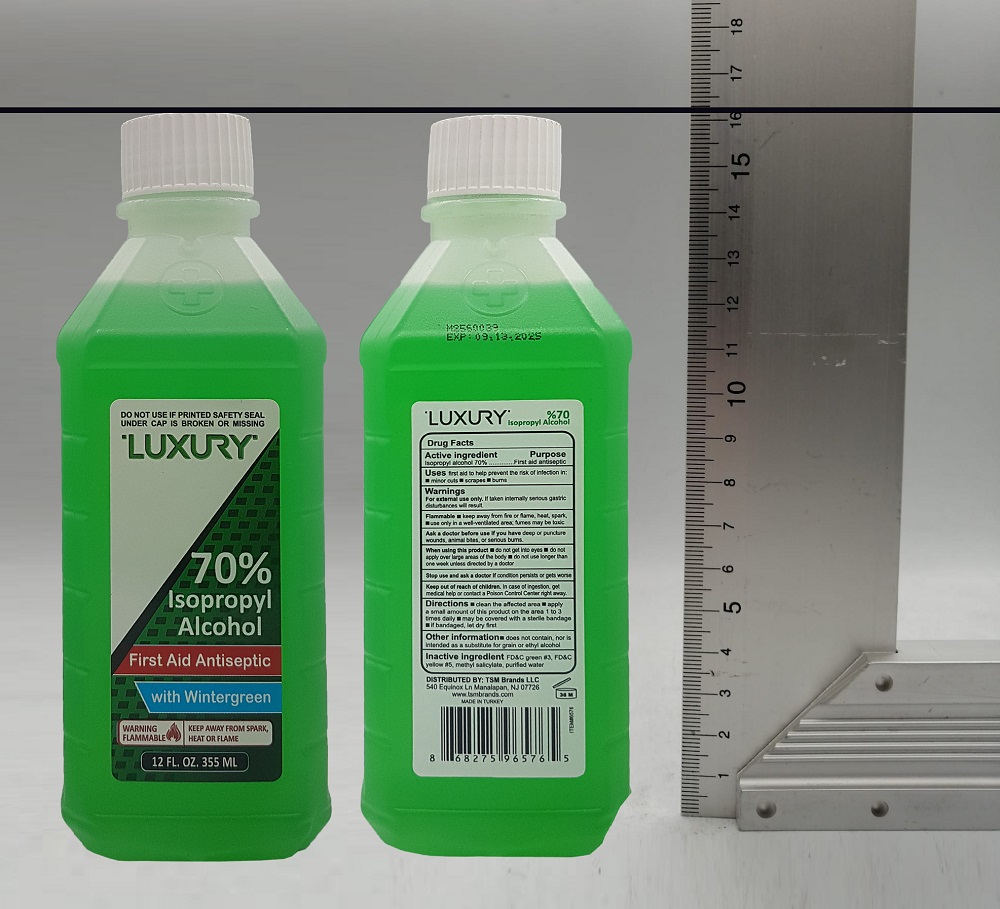 DRUG LABEL: Luxury
NDC: 76772-036 | Form: SOLUTION
Manufacturer: TSM ITHALAT IHRACAT SANAYI VE DIS TICARET LIMITED SIRKETI
Category: otc | Type: HUMAN OTC DRUG LABEL
Date: 20220127

ACTIVE INGREDIENTS: ISOPROPYL ALCOHOL 70 mL/100 mL
INACTIVE INGREDIENTS: FD&C GREEN NO. 3; FD&C YELLOW NO. 5; METHYL SALICYLATE; WATER

Luxury 70% Isopropyl Alcohol- with Wintergreen

Active ingredient

Isopropyl Alcohol 70%

Purpose

First Aid Antiseptic

Uses

First aid to help prevent the risk of infection in:

- minor cuts
- scrapes
- burns

Warnings

For external use only.

If taken internally serious gastric

Flammable. Keep away from fire or flame, heat, spark, electrical.

Ask a doctor before use if you have deep puncture wounds, animal bites or serious burns.

When using this product

- do not get into eyes
- do not inhale
- do not apply over large areas of the body
- do not use longer than 1 week

Keep out of reach of children. If swallowed, get medical help or contact a Poison Control Center right away.

Directions

- clean the affected area
- apply a small amount of this product on the area 1 to 3 times daily
- may be covered with a sterile bandage
- if bandaged, let dry first

Other information

- does not contain, nor is intended as a substitute for grain or ethyl alcohol

Inactive ingredient

purified water, FD&C green #3, FD&C yellow #5, methyl salicylate